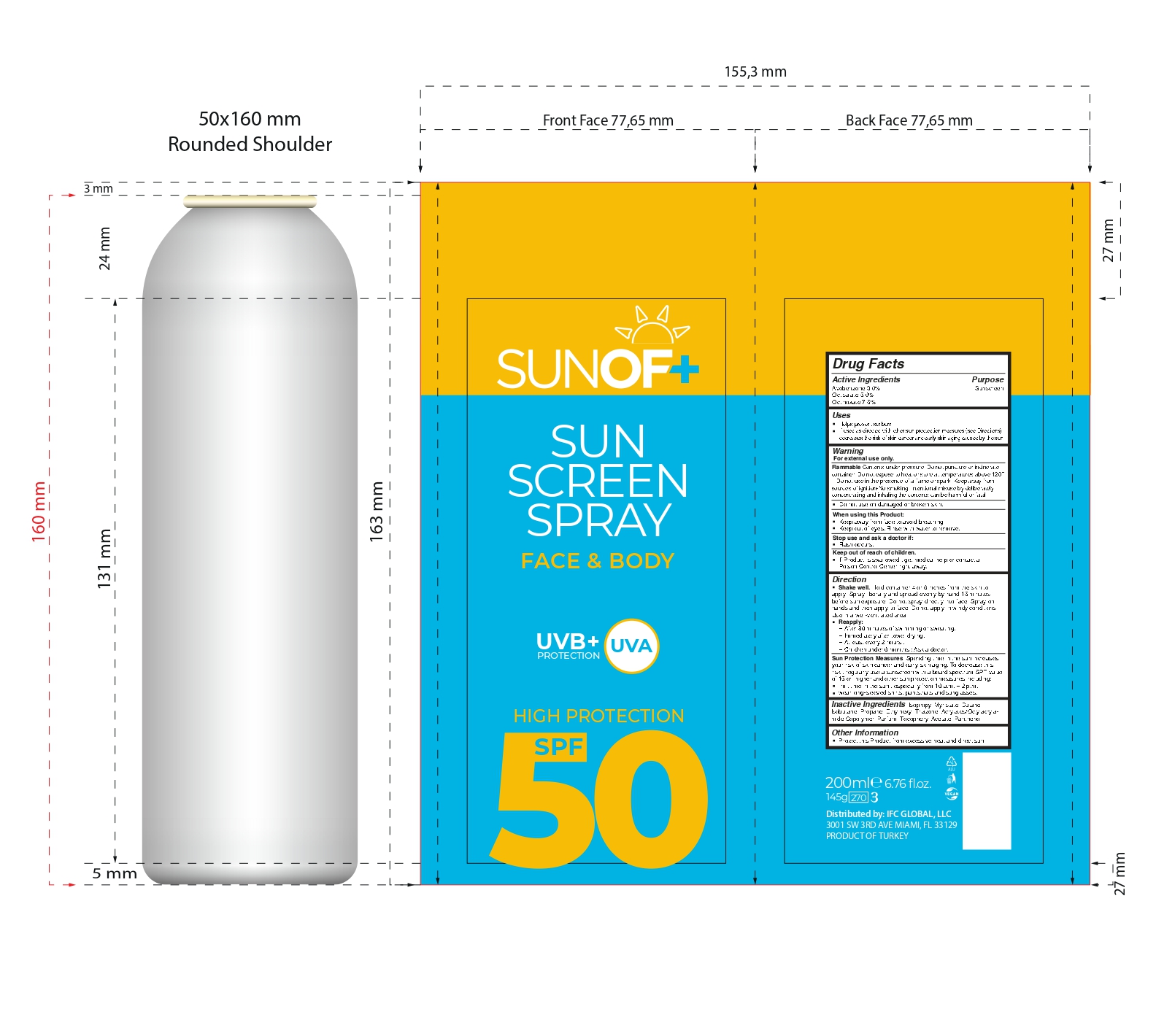 DRUG LABEL: SUNOF Sunscreen SPF 50
NDC: 77418-003 | Form: AEROSOL
Manufacturer: ATAK FARMA KOZMETIK VE KIMYA SANAYI TICARET ANONIM SIRKETI
Category: otc | Type: HUMAN OTC DRUG LABEL
Date: 20250105

ACTIVE INGREDIENTS: OCTINOXATE 7.5 g/100 mL; AVOBENZONE 3 g/100 mL; OCTISALATE 5 g/100 mL
INACTIVE INGREDIENTS: DENATONIUM BENZOATE; PARFUMIDINE; ISOPROPYL MYRISTATE; ISOBUTANE; ETHYLHEXYL TRIAZONE; .ALPHA.-TOCOPHEROL ACETATE, D-; PANTHENOL; ACRYLATES/OCTYLACRYLAMIDE COPOLYMER (75000 MW); 1,3-BIS(DIPHENYLPHOSPHINO)PROPANE; 1,3-BUTANEDITHIOL

Inactive Ingredients

Alcohol Denat. , Isopropyl Myristate , Butane , Isobutane , Propane , Ethylhexyl Triazone

Acrylates/Octylacrylamide Copolymer , Parfum , Tocopheryl Acetate , Panthenol

WARNINGS

For external use only.

Do not use on damaged or broken skin.

When using this Product Keep away from face to avoid breathing it

Keep out of eyes.Rinse with water to remove.

Stop use and ask a doctor if rash occurs.

Active Ingredients

Avobenzone 3.0%

Octisalate 5.0%

Octinoxate 7.5%

Flammable

Contents under pressure. Do not puncture or incinerate container. Do not expose to heat or store at temperatures above 120 F . Do not use in the presence of a flame or spark . Keep away from sources of ignition-No smoking . Intentional misuse by deliberately concentrating and inhaling the contents can be harmful or fatal.

Keep out of reach of children.

If Product is swallowed , get medical help or contact a Poison Control Center right away.

Directions

Shake well . Hold container 4 or 6 inches from the skin to apply. Spray liberally and spread evenly by hand 15 minutes before sun exposure. Do not spray directly into face. Spray on hands and then apply to face. Do not apply in windy conditions. Use in a well-ventilated area.Reapply : after 80 minutes of swimming or sweating.Immediately after towel drying. At least every 2 hours . Children under 6 months : Ask a doctor. Sun Protection Measures . Spending time in the sun increases your risk of skin cancer and early skin aging. To decrease this risk , regularly use a sunscreen with a board spectrum SPF value of 15 or higher and other sun protection measures including: limit time in the sun , especially from 10 a.m. – 2 p.m. wear long-sleeved shirts, pants,hats and sunglasses.

Uses

Helps prevent sunburn

If used as directed with other sun proctection measures (see Directions), decreases the risk of skin cancer and early skin aging caused by the sun.

PURPOSE

Helps prevent sunburn